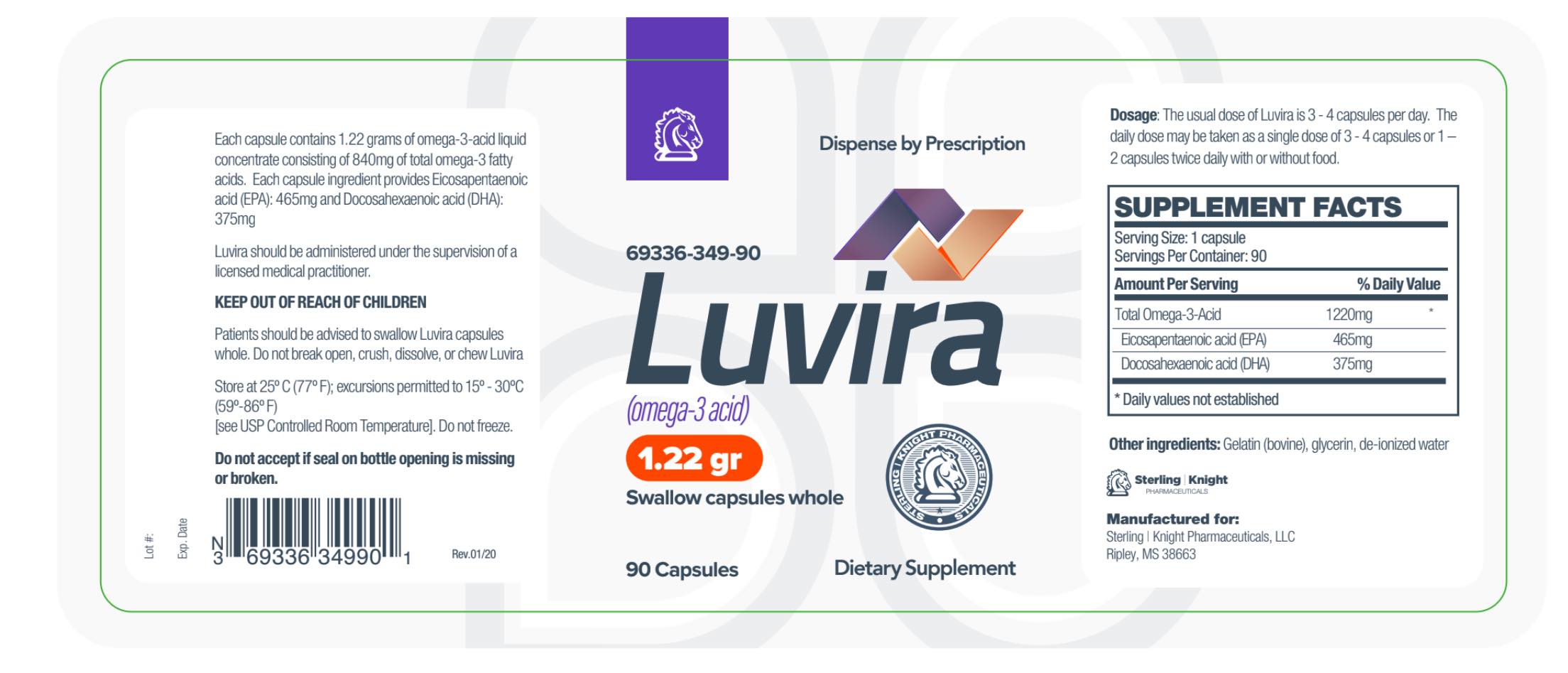 DRUG LABEL: Luvira
NDC: 69336-349 | Form: CAPSULE
Manufacturer: Sterling-Knight Pharmaceuticals, LLC
Category: prescription | Type: HUMAN PRESCRIPTION DRUG LABEL
Date: 20200128

ACTIVE INGREDIENTS: OMEGA-3 FATTY ACIDS 1220 mg/1 1; 12-HYDROXYEICOSAPENTAENOIC ACID, (12R)- 465 mg/1 1; 4,7,10,13,16,19-DOCOSAHEXAENOIC ACID, (4E,7E,10E,13E,16E,19E)- 375 mg/1 1
INACTIVE INGREDIENTS: GELATIN; GLYCERIN

Luvira Capsules
Omega-3-acid
Dietary Supplement
Dispense by Prescription

DESCRIPTION

Luvira is an orally administered prescription omega-3-acid dietary supplement formulation for the clinical dietary management of suboptimal nutritional status in patients where advanced supplementation is required and nutritional supplementation in physiologically stressful conditions for maintenance of good health is needed.

Luvira should be administered under the supervision of a licensed medical practitioner.

SUPPLEMENT FACTS

Serving Size: 1 Capsule

Servings Per Container:90

Amount Per Serving%Daily Value

Total Omega-3-Acid 1220mg*

Eicosapentaenoic acid (EPA) 465 mg

Docosahexaenoic acid(DHA) 375 mg

*Daily values not established

Other Ingredients: Gelatin (bovine), glycerin, de-ionized water.

INDICATIONS AND USAGE

Luvira is an orally administered prescription omega-3-acid formulation for the clinical dietary management of suboptimal nutritional status in patients where advanced supplementation is required and nutritional supplementation in physiologically stressful conditions for maintenance of good health is needed.

WARNINGS AND PRECAUTIONS:

This product is contraindicated in patients with a known hypersensitivity to any of the ingredients.
Luvira should only be used under the direction and supervision of a licensed medical practitioner. Use with caution in patients that may have a medical condition, are pregnant, lactating, trying to conceive, under the age of 18, or taking medications.

DOSAGE AND ADMINISTRATION

The usual dose of Luvira is 3 - 4 capsules per day.
The daily dose may be taken as a single dose of 3 - 4 capsules or 1 – 2 capsules twice daily with or without food.

HOW SUPPLIED

Luvira is supplied as clear yellowish Softgel capsule dispensed in white HDPE plastic bottles of 90ct.
69336-349-90

STORAGE AND HANDLING

Store at controlled room temperature 15°-30°C (59°F-86°F). Keep in cool dry place. Call your doctor about side effects. You may report side effects to FDA at 1-800-FDA-1088. KEEP THIS OUT OF THE REACH OF CHILDREN.

Reserved for Professional Recommendation
All prescriptions using this product shall be pursuant to state statutes as applicable. This is not an Orange Book product. This product may be administered only under a physician’s supervision. There are no implied or explicit claims on therapeutic equivalence.

Manufactured for:
Sterling-Knight Pharmaceuticals, LLC
Ripley, MS 38663
Item 34990
Rev. 0620-1